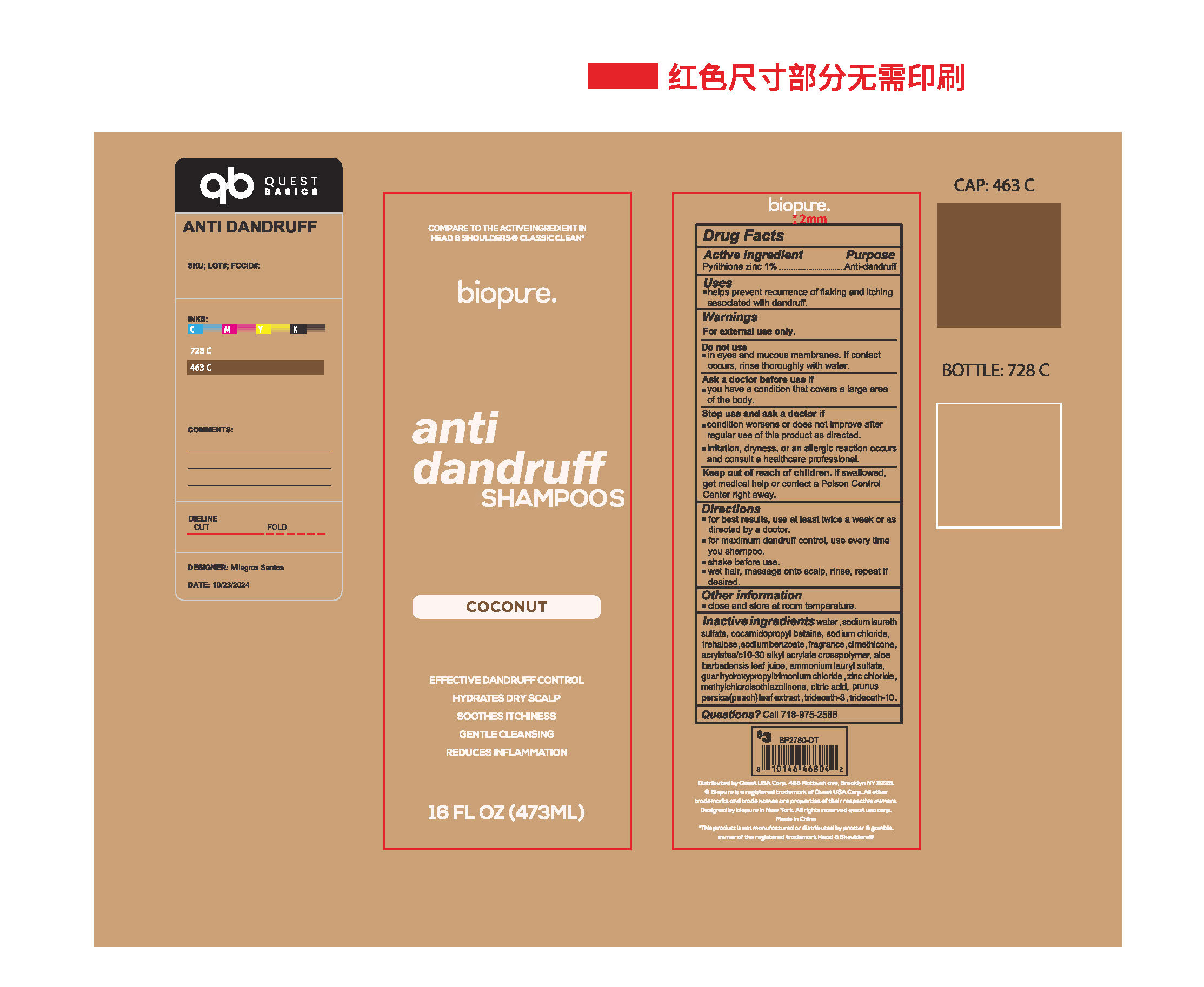 DRUG LABEL: anti dandruff SHAMPOOS
NDC: 85434-002 | Form: LIQUID
Manufacturer: Guangdong Quaker Daily Chemical Co., LTD
Category: otc | Type: HUMAN OTC DRUG LABEL
Date: 20250326

ACTIVE INGREDIENTS: PYRITHIONE ZINC 1 g/100 mL
INACTIVE INGREDIENTS: COCAMIDOPROPYL BETAINE; FRAGRANCE 13576; SODIUM LAURETH SULFATE; AMMONIUM LAURYL SULFATE; PRUNUS PERSICA LEAF; TREHALOSE; GUAR HYDROXYPROPYLTRIMONIUM CHLORIDE; ACRYLATES/C10-30 ALKYL ACRYLATE CROSSPOLYMER (60000 MPA.S); METHYLCHLOROISOTHIAZOLINONE; SODIUM BENZOATE; ALOE BARBADENSIS LEAF POWDER; SODIUM CHLORIDE; TRIDECETH-10; CITRIC ACID; TRIDECETH-3; DIMETHICONE; WATER; ZINC CHLORIDE

anti dandruff SHAMPOOS

ACTIVE INGREDIENT

Pyrithione zinc 1%

PURPOSE

Anti-dandruff

INDICATIONS AND USAGE

helps prevent recurence of flaking and itchingassociated with dandruff

WARNINGS

For external uae only.

DO NOT USE

in eyes and mucous membranes. lf contactoccurs, rinse thoroughly with water.

WHEN USING

you have a conditon that covers a large area of the body.

STOP USE

condltlan worsens or does not lmprove afterregular use of thls product as dlrected.
iritation, dryness, or an allergic reaction occursand consult a healtheare professional.

KEEP OUT OF REACH OF CHILDREN

Keep out of roach of chlldren. lf swallowed.get medlcal help or contact a Pokson ControlCanter rlght away

DOSAGE AND ADMINISTRATION

for best results, use at least twice a week or asdirectad by a doctor.
for maxmum dandruff control, use every tmeyou shampoo
shake before use.
wet halr, massage onto scalp, rinse, repeat lf desired.

INACTIVE INGREDIENT

water
sodium laureth sulfate
cocamidopropyl betaine
guar hydroxypropyltrimonium chloride
acrylates/c10-30 alkyl acrylate crosspolymer
zinc chloride
sodium chloride
methylchloroisothiazolinone
dimethicone
trideceth-3
trideceth-10
citric acid
prunus persica (peach) leaf extract
trehalose
aloe barbadensis leaf juice
ammonium lauryl sulfate
sodium benzoate
fragrance